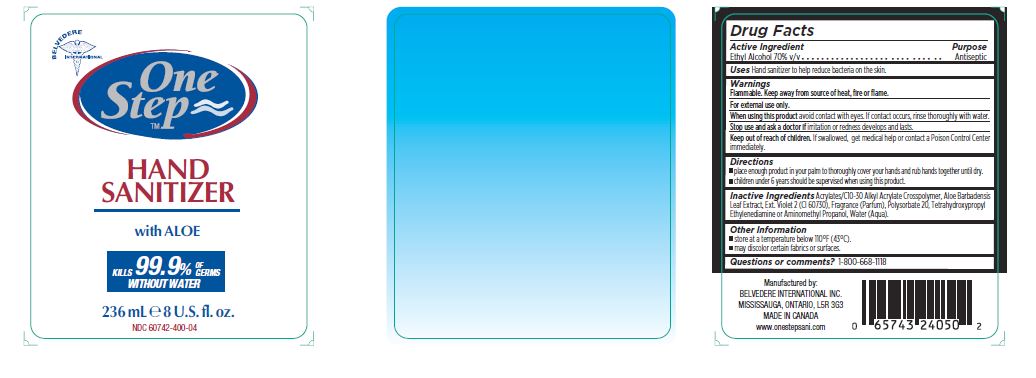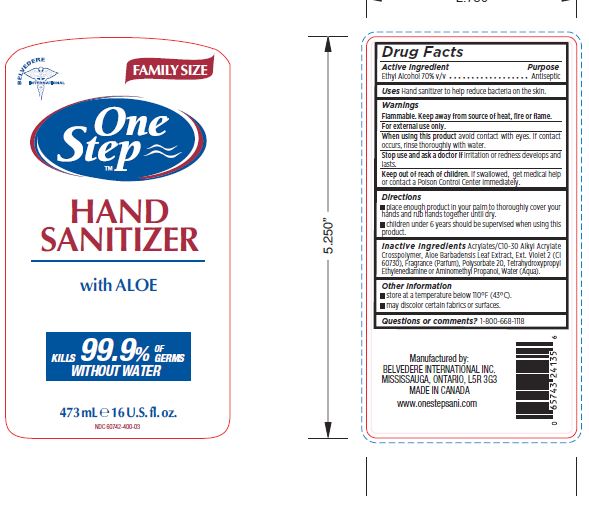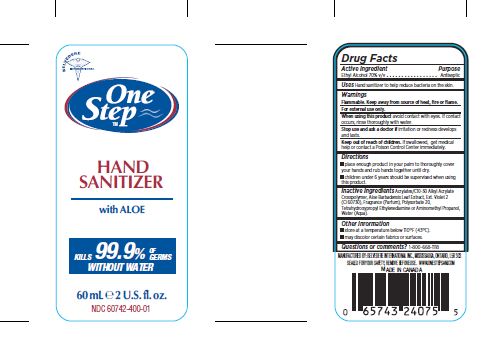 DRUG LABEL: ONE STEP
NDC: 60742-400 | Form: GEL
Manufacturer: BELVEDERE INTERNATIONAL INC.
Category: otc | Type: HUMAN OTC DRUG LABEL
Date: 20200203

ACTIVE INGREDIENTS: ALCOHOL 70 mL/100 mL
INACTIVE INGREDIENTS: EDETOL; CARBOMER 940; ALOE VERA LEAF; POLYSORBATE 20; EXT. D&C VIOLET NO. 2; WATER

ONE STEP HAND SANITIZER

Active Ingredient

Ethyl Alcohol 70%v/v .........Antiseptic

Uses

Hand sanitizer to help reduce bacteria on the skin

Warnings

Flammable. Keep away from source of heat, fire or flame.

For external use only.

Stop use and ask a doctor if irritation or redness develops and lasts.

When using this product avoid contact with eyes. if contact occurs, rinse thoroughly with water.

Keep out of reach of children. If swallowed get medical help or contact a Poison Control Center immediately.

Directions

Place enough product in your palm to thoroughly cover your hands and rub hands together until dry.

Children under 6 years should be supervised when using this product.

Inactive Ingredients

Acrylates/C10-30 Alkyl Acrylate Crosspolymer, Aloe Barbadensis Leaf Extract, Ext. Violet 2 (CI 60730), Fragrance (Parfum), Polysorbate 20, Tetrahydroxypropyl Ethylenediamine, Water (Aqua).

OTHER SAFETY INFORMATION

Store at a temperature below 110 F (43oC)

may discolor certain fabrics or surfaces.

DOSAGE AND ADMINISTRATION

Children under 6 years should be supervised when using this product